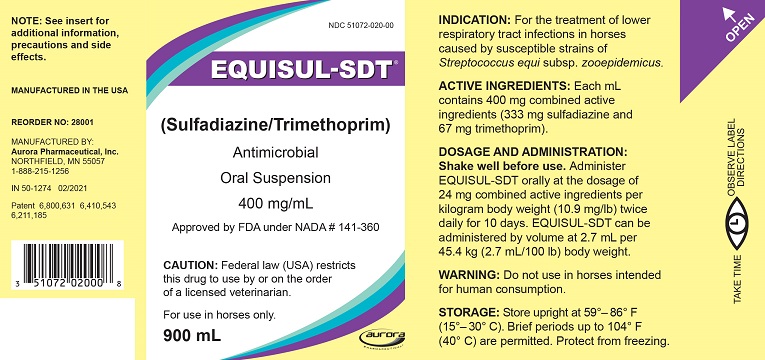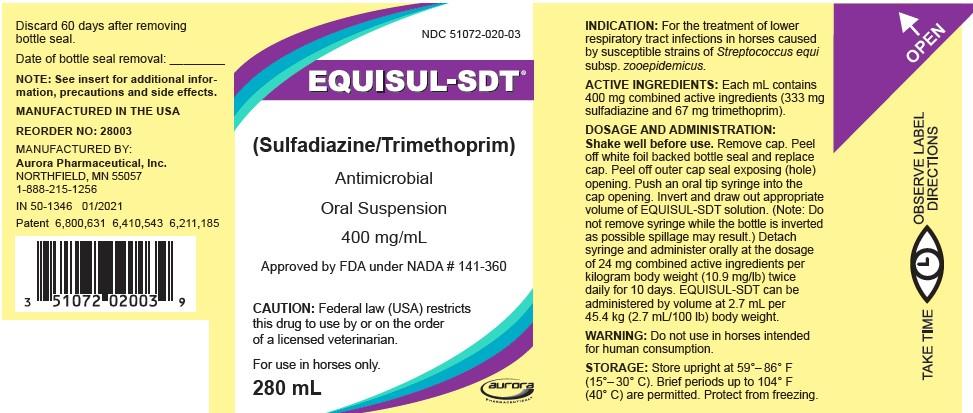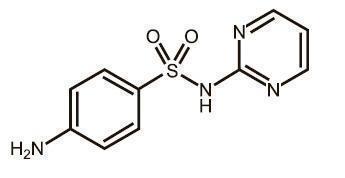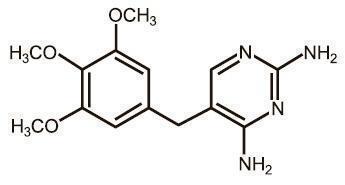 DRUG LABEL: Equisul-SDT
NDC: 51072-020 | Form: SUSPENSION
Manufacturer: Aurora Pharmaceutical, Inc.
Category: animal | Type: PRESCRIPTION ANIMAL DRUG LABEL
Date: 20250616

ACTIVE INGREDIENTS: SULFADIAZINE 333 mg/1 mL; TRIMETHOPRIM 67 mg/1 mL

EQUISUL-SDT®
(Sulfadiazine/Trimethoprim)
Oral Suspension

For use in horses only.

Approved by FDA under NADA # 141-360

CAUTION

Federal law (USA) restricts this drug to use by or on the order of a licensed veterinarian.

DESCRIPTION

EQUISUL-SDT is a broad-spectrum antimicrobial from the potentiated sulfonamide class of chemotherapeutic agents. These two drugs block different sequential steps in the biosynthesis of nucleic acids. Sulfadiazine inhibits bacterial synthesis of dihydrofolic acid by competing with para-aminobenzoic acid. Trimethoprim blocks the production of tetrahydrofolic acid from dihydrofolic acid by reversibly inhibiting dihydrofolate reductase. The effect of the dual action is to reduce the minimum inhibitory concentration of each agent (synergism) and to convert a bacteriostatic action to a bactericidal action. Sulfadiazine is the non-proprietary name for 4-amino-N-2-pyrimidinylbenzenesulfonamide. Trimethoprim is the non-proprietary name for 5-[(3,4,5¬trimethoxyphenyl) methyl]-2,4-pyrimidinediamine.

Figure 1. Structure of sulfadiazine

Figure 2. Structure of trimethoprim

Each mL of EQUISUL-SDT contains 400 mg combined active ingredients (333 mg sulfadiazine and 67 mg trimethoprim) in an aqueous suspension.

INDICATION

EQUISUL-SDT is indicated for the treatment of lower respiratory tract infections in horses caused by susceptible strains of Streptococcus equi subsp. zooepidemicus.

DOSAGE AND ADMINISTRATION

Shake well before use.

Administer EQUISUL-SDT orally at the dosage of 24 mg combined active ingredients per kilogram body weight (10.9 mg/lb) twice daily for 10 days. EQUISUL-SDT can be administered by volume at 2.7 mL per 45.4 kg (2.7 mL/100 lb) body weight.

For 280 mL and 560 mL bottles with draw-off cap:

Remove cap. Peel off white foil backed bottle seal and replace cap. Peel off outer cap seal exposing (hole) opening. Push an oral tip syringe into the cap opening. Invert and draw out appropriate volume of EQUISUL-SDT solution. (Note: Do not remove syringe while the bottle is inverted as possible spillage may result.) Detach syringe and administer orally at the dosage of 24 mg combined active ingredients per kilogram body weight (10.9 mg/lb) twice daily for 10 days. EQUISUL-SDT can be administered by volume at 2.7 mL per 45.4 kg (2.7 mL/100 lb) body weight.

CONTRAINDICATIONS

EQUISUL-SDT is contraindicated in horses with a known allergy to sulfadiazine, sulfonamide class antimicrobials, or trimethoprim.

WARNING

Do not use in horses intended for human consumption.

HUMAN WARNINGS

Not for use in humans. For use in animals only. Keep this and all drugs out of the reach of children. Consult a physician in the case of accidental human exposure.

Antimicrobial drugs, including sulfonamides, can cause mild to severe allergic reactions in some individuals. Avoid direct contact of the product with the skin, eyes, mouth, and clothing. Persons with a known sensitivity to sulfonamides or trimethoprim should avoid exposure to this product. If an allergic reaction occurs (e.g., skin rash, hives, difficulty breathing, facial swelling) seek medical attention.

PRECAUTIONS

Prescribing antibacterial drugs in the absence of a proven or strongly suspected bacterial infection is unlikely to provide benefit to treated animals and may increase the risk of development of drug-resistant animal pathogens.

The administration of antimicrobials, including sulfadiazine and trimethoprim, to horses under conditions of stress may be associated with acute diarrhea that can be fatal. If acute diarrhea or persistent changes in fecal consistency are observed, additional doses of EQUISUL-SDT should not be administered and appropriate therapy should be initiated.

The safe use of EQUISUL-SDT has not been evaluated in breeding, pregnant, or lactating horses. Potentiated sulfonamides should only be used in pregnant or lactating mares when the benefits to the mare justify the risks to the fetus. Use of potentiated sulfonamides during pregnancy has been associated with an increased risk of congenital abnormalities that may be related to folate deficiency. In humans, sulfonamides pass through the placenta, are excreted in milk, and may cause hyperbilirubinemia-induced neurotoxicity in nursing neonates.

Decreased hematopoetic activity and blood dyscrasias have been associated with the use of elevated doses and/or prolonged administration of potentiated sulfonamides. EQUISUL-SDT should be discontinued if prolonged clotting times, or decreased platelet, white blood cell or red blood cell counts are observed.

Sulfonamides should be used with caution in horses with impaired hepatic function. Although rare, sulfonamide use has been associated with fulminant hepatic necrosis in humans.

Neurologic abnormalities have been reported in several species following administration of potentiated sulfonamides. In horses, potentiated sulfonamides have been associated with gait alterations and behavior changes that resolved after discontinuation of the drug.

The safe use of EQUISUL-SDT has not been evaluated in horses less than 1 year of age.

ADVERSE REACTIONS

Adverse reactions reported during a field study of 270 horses of various breeds, ranging from 1 to 25 years of age, which had been treated with either EQUISUL-SDT (n = 182) or with a saline control (n = 88) are summarized in Table 1. At least one episode of loose stool of varying severity was observed in 69 of 182 (38%) of the EQUISUL-SDT-treated horses, and 29 of 88 (33%) saline control horses. Of those animals experiencing loose stool, 2 of 182 (1.1%) of the EQUISUL-SDT-treated horses and 0 of 88 (0%) placebo-treated horses were removed from the study due to diarrhea (defined as at least one episode of watery stool). Both cases of diarrhea in this study were self-limiting and resolved without treatment within 5–10 days after discontinuation of EQUISUL-SDT.

Table 1. Number of Horses with Adverse Reactions During the Field Study with EQUISUL-SDT
Adverse Reactions | Equisul-SDT (n=182) | Saline control (n=88)
Loose stool (including diarrhea) | 69 (38%) | 29 (33%)
Colic | 3 (1.6%) | 2 (2.2%)
Diarrhea | 2 (1.1%) | 0 (0%)

To report suspected adverse events, for technical assistance or to obtain a copy of the SDS, contact Aurora Pharmaceutical, Inc. at 1-888-215-1256 or www.aurorapharmaceutical.com. For additional information about adverse drug experience reporting for animal drugs, contact FDA at 1-888-FDA-VETS or online at www.fda. gov/reportanimalae.

CLINICAL PHARMACOLOGY

Following oral administration, EQUISUL-SDT is rapidly absorbed and widely distributed throughout body tissues. Sulfadiazine levels are usually highest in the kidney, while the tissue concentration in other tissues is only slightly lower than plasma concentrations. Concentrations of trimethoprim are usually higher in the lungs, kidney, and liver than in the blood. Sulfadiazine and trimethoprim are both eliminated primarily by renal excretion, both by glomerular filtration and tubular secretion. Urine concentrations of both sulfadiazine and trimethoprim are several-fold higher than blood concentrations. [Kahn CM, Line S, eds. The Merck Veterinary Manual. 10th Ed. Merck & Co. 2010.] Sulfadiazine and trimethoprim are 20% and 35% bound to plasma protein, respectively. Administration of sulfadiazine and trimethoprim with food has no apparent effect on absorption of sulfadiazine but the absorption of trimethoprim is decreased.

Based on a study in fed horses, trimethoprim concentrations following repeat oral administration of 24 mg/kg EQUISUL-SDT to 6 horses reached peak concentration in 0.5 to 12.0 hours. The median plasma elimination half-life was 3 hours, with a range of 2.31 to 4.96 hours. Peak sulfadiazine concentrations were reached within 1.0 to 12.0 hours in the same study. The median plasma elimination half-life for sulfadiazine was approximately 7.80 hours, with a range of 6.78 to 10.39 hours. Only minor accumulation of both drugs was observed following repeat oral administration of EQUISUL-SDT and both drugs reached steady state by day 3. Sulfadiazine and trimethoprim key steady state parameters associated with administration in 6 fed horses over a period of 7 days are found in Table 2.

Table 2. Median (Range) of sulfadiazine and trimethoprim pharmacokinetics parameters following repeat dosing of 24 mg/kg bid EQUISUL-SDT for 7 days to six horses in fed condition
Drug | Sulfadiazine | Trimethoprim
Tmax (hr) | 4.75 (1.0012.00) | 8.50 (0.5012.00)
Cmax (µg/mL) | 17.63 (10.1031.15) | 0.78 (0.601.14)
AUC 012 (last dose) (hr*µg/mL) | 159.35 (73.90282.54) | 5.47 (3.3110.91)
T 1/2 (hr) | 7.80 (6.7810.39) | 3.00 (2.314.96)

MICROBIOLOGY

EQUISUL-SDT is the combination of the sulfonamide sulfadiazine and trimethoprim. These two drugs block sequential steps in nucleic acids biosynthesis. Sulfadiazine inhibits bacterial synthesis of dihydrofolic acid by competing with para-aminobenzoic acid. Trimethoprim blocks the production of tetrahydrofolic acid from dihydrofolic acid by reversibly inhibiting dihydrofolate reductase. The two drugs act synergistically, reducing the minimum inhibitory concentration of each, while enhancing the bacteriostatic action of each separately to a bactericidal action when combined.

EQUISUL-SDT administered as a combined sulfadiazine-trimethoprim dose of 24 mg/kg body weight twice daily for 7 days provided concentrations of sulfadiazine and trimethoprim with T>MIC90 (%T) values of 100% and 98% respectively. The minimum inhibitory concentration (MIC) values for EQUISUL-SDT against indicated pathogens isolated from lower respiratory tract infections in horses enrolled in a 2010–2011 effectiveness field study are presented in Table 3. All MICs were determined in accordance with the Clinical and Laboratory Standards Institute (CLSI) Approved Standard M31-A3 using a broth microdilution system and 3% lysed horse blood.

Table 3. Trimethoprim/sulfadiazine minimum inhibitory concentration (MIC) values [The correlation between in vitro susceptibility data and clinical effectiveness is unknown.] of isolates recovered from horses with lower respiratory infection caused by Streptococcus equi subsp. zooepidemicus treated with EQUISUL-SDT in the U.S. (2010–2011)
Treatment Outcome | Success | Failure
Number of Isolates | 65 [One isolate of S. equi subsp. zooepidemicus was not tested.] | 46
Time of Sample Collection | Pre-Treatment | Pre-Treatment
MIC 50 [The lowest MIC to encompass 50% and 90% of the most susceptible isolates, respectively.] (µg/mL) | 0.25/4.75 | 0.25/4.75
MIC 90 (µg/mL) | 0.25/4.75 | 0.25/4.75
MIC Range (µg/mL) | 0.12/2.4 to 0.5/9.5 | 0.12/2.4 to 0.5/9.5

EFFECTIVENESS

A negative control, randomized, masked, field study evaluated the effectiveness of EQUISUL-SDT administered at 24 mg/kg body weight, orally, twice daily for 10 days for the treatment of lower respiratory tract infections in horses caused by Streptococcus equi subsp. zooepidemicus. In this study, a total of 182 horses were treated with EQUISUL-SDT, and 88 horses were treated with saline. One hundred seventy-three horses (112 EQUISUL-SDT and 61 saline) were included in the statistical analysis. Therapeutic success was characterized by absence of fever and no worsening of clinical signs at Day 5 and Day 10, and significant clinical improvement or resolution of clinical signs of lower respiratory tract infection by Day 17. The observed success rates are 58.9% (66/112) and 14.8% (9/61) for the EQUISUL-SDT and saline-treated groups, respectively.

Table 4 summarizes the statistical analysis results on the overall success rate.

Table 4. Overall Clinical Effectiveness Results
 | Equisul-SDT | Saline | P-value [P-value and estimated success rates are based on back-transformed mean estimates from the statistical analysis.]
Least Square Means | 61% | 13.1% | 0.0123

ANIMAL SAFETY

In a target animal safety study, EQUISUL-SDT was administered orally to 32 healthy adult horses at 0 (0×), 24 (1×), 72 (3×), or 120 (5×) mg/kg twice daily for 30 days. Loose stool was the most common abnormal observation. Observations of loose stool (pellets with liquid or unformed/cowpile stool) occurred more often in horses treated with EQUISUL-SDT with the incidence of loose stool increasing in a dose related manner. All incidents of loose stool were self-limiting and resolved without treatment.

Horses in all EQUISUL-SDT groups demonstrated statistically significantly higher mean serum creatinine concentrations, and those in the 3× and 5× groups demonstrated statistically significantly higher mean serum albumin concentrations. Statistically higher mean neutrophil counts and mean serum gamma glutamyl transferase (GGT) activity were seen in the 1× and 5× groups. Individual animal creatinine, GGT, and albumin concentrations remained within the reference range. Individual animal elevations in absolute neutrophil counts ranged up to 7.09 × 10^3/mcL (reference range: 1.96-5.31 × 10^3/mcL).

Based upon blood concentrations obtained during the study, it was noted that the sulfadiazine and trimethoprim plasma concentrations did not increase in proportion to dose. For sulfadiazine, a 3× and 5× dose resulted in an average exposure of 2.0× and 2.6× the concentrations observed following a 1× dose. For trimethoprim, the corresponding values were 2.5× and 3.5× as compared to the 1× dose. Furthermore, marked intersubject variability, particularly with sulfadiazine, resulted in substantial overlap of individual subject blood levels across the three dosing groups.

STORAGE CONDITIONS

Store upright at 59°– 86° F (15°– 30° C). Brief periods up to 104° F (40° C) are permitted. Protect from freezing.

HOW SUPPLIED

EQUISUL-SDT is available in the following package sizes:
135 mL
280 mL
560 mL
900 mL

MANUFACTURED IN THE USA

MANUFACTURED BY:

Aurora Pharmaceutical, Inc.

NORTHFIELD, MN 55057

1-888-215-1256

Patent 6,800,631 6,410,543 6,211,185

Note: See insert for additional information, precautions and side effects

PRINCIPAL DISPLAY PANEL - 900 mL Bottle Label

NDC 51072-020-00

EQUISUL-SDT®

(Sulfadiazine/Trimethoprim)

Antimicrobial

Oral Suspension

400 mg/mL

Approved by FDA under NADA # 141-360

CAUTION: Federal law (USA) restricts this drug to use by or on the order of a licensed veterinarian.

For use in horses only.

900 mL

REORDER No: 28001

IN 50-1274 02/2021

aurora pharmaceutical®

PRINCIPAL DISPLAY PANEL - 280 mL Bottle Label with draw-off cap

NDC 51072-020-03

EQUISUL-SDT®

(Sulfadiazine/Trimethoprim)

Antimicrobial

Oral Suspension

400 mg/mL

Approved by FDA under NADA # 141-360

CAUTION: Federal law (USA) restricts this drug to use by or on the order of a licensed veterinarian.

For use in horses only.

280 mL

REORDER No: 28003

IN 50-1346 01/2021

aurora pharmaceutical®